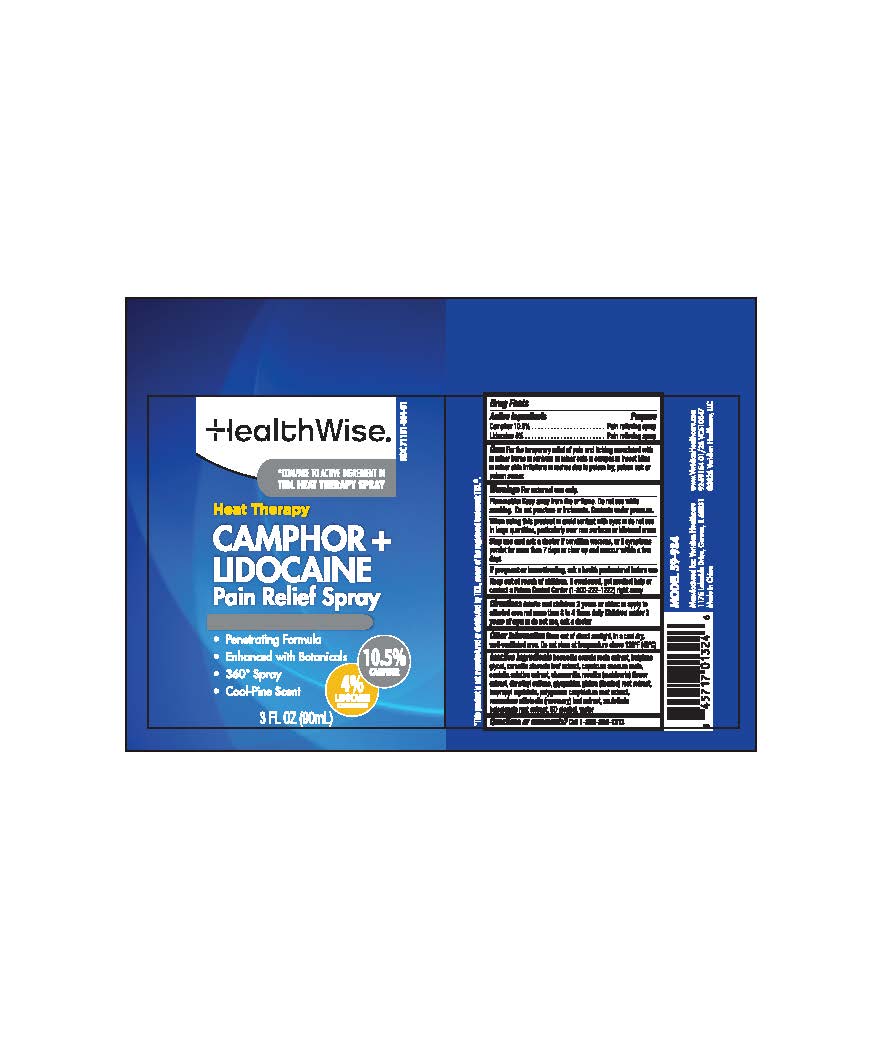 DRUG LABEL: Camphor plus Lidocaine Pain Relief
NDC: 71101-984 | Form: SPRAY
Manufacturer: Veridian Healthcare
Category: otc | Type: HUMAN OTC DRUG LABEL
Date: 20260206

ACTIVE INGREDIENTS: CAMPHOR (NATURAL) 10.5 g/100 mL; LIDOCAINE 4 g/100 mL
INACTIVE INGREDIENTS: BUTYLENE GLYCOL; BOSWELLIA SERRATA GUM; PAPRIKA OIL; ISOPROPYL MYRISTATE; ALCOHOL; DIMETHYL SULFONE; WATER; CENTELLA ASIATICA; CHAMOMILE; SCUTELLARIA BAICALENSIS ROOT; POLYGONUM CUSPIDATUM ROOT; WHITE TEA; GLYCYRRHIZA GLABRA (LICORICE) ROOT POWDER; ROSEMARY

HealthWise Camphor + Lidocaine Spray

Drug Facts

Active Ingredients

Camphor 10.5%
Lidocaine 4%

Purpose

Pain relieving spray

Uses

for temporary relief of pain and itching associated with:

- minor burns
- sunburns
- minor cuts
- scrapes
- insect bites
- minor skin irritations
- rashes due to poison ivy, poison oak or poison sumac

Warnings

For external use only

Flammable Do not use while smoking or near heat of flame. Do not use while smoking. Do not punture or incinerate. Contents under pressure.

When using this product

- avoid contact with eyes
- do not use in large quantities, particularly over raw surfaces or blistered areas.

Stop use and ask a doctor if

condition worsens or if symptoms persist for more than 7 days or clear up and reoccur within a few days.

If pregnant or breastfeeding

ask a health professional before use

Keep out of reach of children.

If swallowed, get medical help or contact a Poison Control Center (1-800-222-1222) right away.

Directions

- adults and children 2 years and older:apply to affected area not more than 3 to 4 times daily.
- children under 2 years of age:do not use, ask a doctor

Other information

- Store out of direct sunlight, in a cool dry well-ventilated area. Do not store at temperature above 120F (49C)

Inactive ingredients

boswella serrata resin extract, butylene glycol, camellia sinesis leaf extract, capsicum annuum resin, centella asiatica extract, camomilla recutita (matricaria) flower extract, dimethyl sulfone, glycyrrhiza glabra (licorice) root extract, isopropyl myristate, polygonum cuspidatum root extract, rosmatinus officinalis (rosemary) leaf extract, scutellaria baicalensis root extract, SD alcohol, water